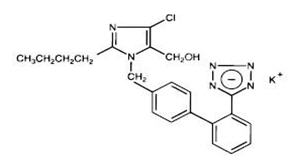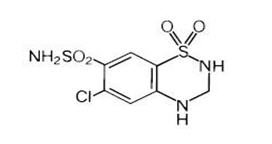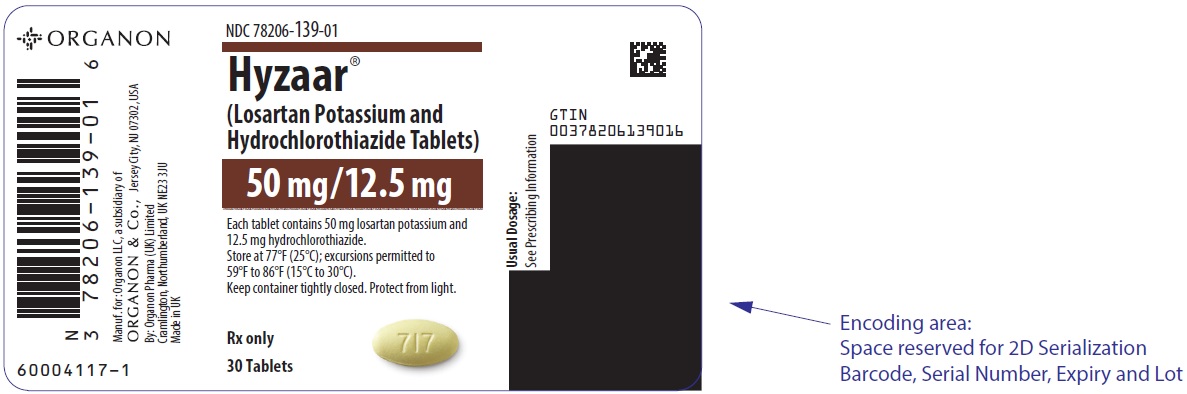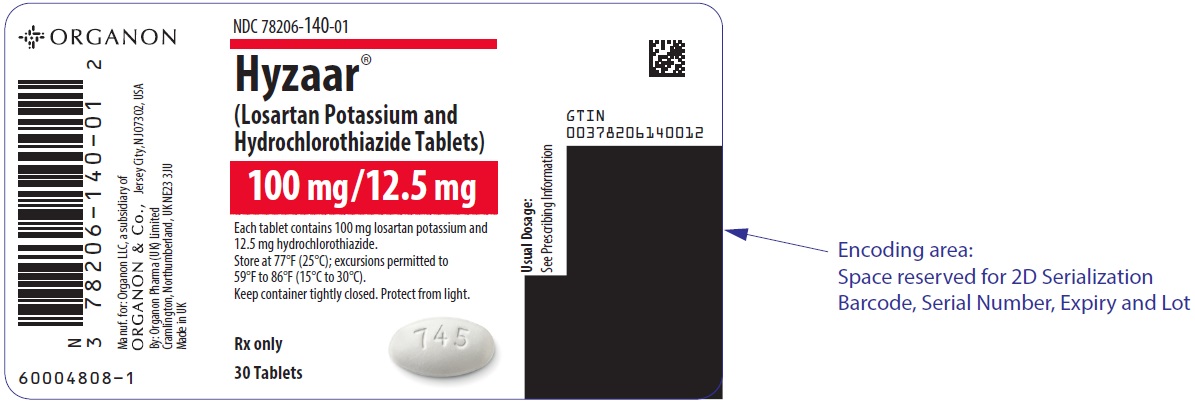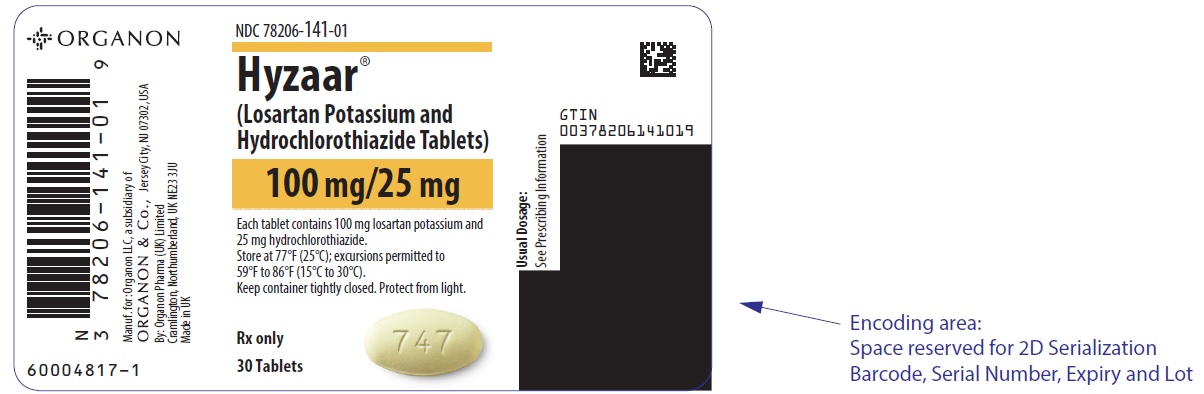 DRUG LABEL: HYZAAR
NDC: 78206-139 | Form: TABLET, FILM COATED
Manufacturer: Organon LLC
Category: prescription | Type: HUMAN PRESCRIPTION DRUG LABEL
Date: 20251126

ACTIVE INGREDIENTS: losartan potassium 50 mg/1 1; hydrochlorothiazide 12.5 mg/1 1
INACTIVE INGREDIENTS: MICROCRYSTALLINE CELLULOSE; LACTOSE MONOHYDRATE; STARCH, CORN; MAGNESIUM STEARATE; HYDROXYPROPYL CELLULOSE (1600000 WAMW); HYPROMELLOSE, UNSPECIFIED; TITANIUM DIOXIDE; D&C YELLOW NO. 10; ALUMINUM OXIDE; CARNAUBA WAX

HIGHLIGHTS OF PRESCRIBING INFORMATION

These highlights do not include all the information needed to use HYZAAR safely and effectively. See full prescribing information for HYZAAR.
HYZAAR® (losartan potassium and hydrochlorothiazide) tablets, for oral use
Initial U.S. Approval: 1995

WARNING: FETAL TOXICITY

See full prescribing information for complete boxed warning.

When pregnancy is detected, discontinue HYZAAR as soon as possible. Drugs that act directly on the renin-angiotensin system can cause injury and death to the developing fetus. (5.1)

1 INDICATIONS AND USAGE

HYZAAR is a combination of losartan, an angiotensin II receptor blocker (ARB) and hydrochlorothiazide, a diuretic indicated for:

- Treatment of hypertension, to lower blood pressure. Lowering blood pressure reduces the risk of fatal and nonfatal cardiovascular events, primarily strokes and myocardial infarctions. (1.1)
- Reduction of the risk of stroke in patients with hypertension and left ventricular hypertrophy. There is evidence that this benefit does not apply to Black patients. (1.2)

2 DOSAGE AND ADMINISTRATION

Hypertension

- Usual starting dose: 50/12.5 mg once daily. (2.1)
- Titrate as needed to a maximum dose of 100/25 mg. (2.1)

Hypertensive Patients with Left Ventricular Hypertrophy

- Not controlled on monotherapy: Initiate with 50/12.5 mg. Titrate as needed to a maximum of 100/25 mg. (2.2)

3 DOSAGE FORMS AND STRENGTHS

Tablets (losartan potassium/hydrochlorothiazide content): 50/12.5 mg; 100/12.5 mg; and 100/25 mg. (3)

4 CONTRAINDICATIONS

- Hypersensitivity to any component of HYZAAR. (4)
- Anuria. (4)
- Coadministration with aliskiren in patients with diabetes. (4)

5 WARNINGS AND PRECAUTIONS

- Hypotension: Correct volume or salt depletion prior to administration of HYZAAR. (5.2)
- Monitor renal function and potassium in susceptible patients. (5.3)
- Observe for clinical signs of fluid or electrolyte imbalance. (5.5)
- Acute angle-closure glaucoma. (5.6)
- Exacerbation of systemic lupus erythematosus. (5.7)

6 ADVERSE REACTIONS

Most common adverse reactions (incidence ≥2% and greater than placebo) are dizziness, upper respiratory infection, cough, and back pain. (6.1)

To report SUSPECTED ADVERSE REACTIONS, contact Organon LLC, a subsidiary of Organon & Co., at 1-844-674-3200 or FDA at 1-800-FDA-1088 or www.fda.gov/medwatch.

7 DRUG INTERACTIONS

- Agents increasing serum potassium: Risk of hyperkalemia. (7.1)
- Lithium: Risk of lithium toxicity. (7.2)
- Non-Steroidal Anti-Inflammatory Drugs (NSAIDs): increased risk of renal impairment and reduced diuretic, natriuretic, and antihypertensive effects. (7.3)
- Dual inhibition of the renin-angiotensin system: increased risk of renal impairment, hypotension, syncope, and hyperkalemia. (7.4)
- Antidiabetic drugs: dosage adjustment of antidiabetic may be required. (7.5)
- Cholestyramine and colestipol: Reduced absorption of thiazides. (7.5)

8 USE IN SPECIFIC POPULATIONS

- Hepatic Impairment: HYZAAR is not recommended for initial therapy, because the recommended starting dose is not available. (8.7)

FULL PRESCRIBING INFORMATION

WARNING: FETAL TOXICITY

When pregnancy is detected, discontinue HYZAAR as soon as possible. Drugs that act directly on the renin-angiotensin system can cause injury and death to the developing fetus [see Warnings and Precautions (5.1)].

1 INDICATIONS AND USAGE

1.1 Hypertension

HYZAAR® is indicated for the treatment of hypertension, to lower blood pressure. Lowering blood pressure lowers the risk of fatal and non-fatal cardiovascular (CV) events, primarily strokes and myocardial infarction. These benefits have been seen in controlled trials of antihypertensive drugs from a wide variety of pharmacologic classes including losartan and hydrochlorothiazide.

Control of high blood pressure should be part of comprehensive cardiovascular risk management, including, as appropriate, lipid control, diabetes management, antithrombotic therapy, smoking cessation, exercise, and limited sodium intake. Many patients will require more than 1 drug to achieve blood pressure goals. For specific advice on goals and management, see published guidelines, such as those of the National High Blood Pressure Education Program's Joint National Committee on Prevention, Detection, Evaluation, and Treatment of High Blood Pressure (JNC).

Numerous antihypertensive drugs, from a variety of pharmacologic classes and with different mechanisms of action, have been shown in randomized controlled trials to reduce cardiovascular morbidity and mortality, and it can be concluded that it is blood pressure reduction, and not some other pharmacologic property of the drugs, that is largely responsible for those benefits. The largest and most consistent cardiovascular outcome benefit has been a reduction in the risk of stroke, but reductions in myocardial infarction and cardiovascular mortality also have been seen regularly.

Elevated systolic or diastolic pressure causes increased cardiovascular risk, and the absolute risk increase per mmHg is greater at higher blood pressures, so that even modest reductions of severe hypertension can provide substantial benefit. Relative risk reduction from blood pressure reduction is similar across populations with varying absolute risk, so the absolute benefit is greater in patients who are at higher risk independent of their hypertension (for example, patients with diabetes or hyperlipidemia), and such patients would be expected to benefit from more aggressive treatment to a lower blood pressure goal.

Some antihypertensive drugs have smaller blood pressure effects (as monotherapy) in Black patients, and many antihypertensive drugs have additional approved indications and effects (e.g., on angina, heart failure, or diabetic kidney disease). These considerations may guide selection of therapy.

This fixed dose combination is not indicated for initial therapy of hypertension, except when the hypertension is severe enough that the value of achieving prompt blood pressure control exceeds the risk of initiating combination therapy in these patients [see Clinical Studies (14) and Dosage and Administration (2.1)].

HYZAAR may be administered with other antihypertensive agents.

1.2 Hypertensive Patients with Left Ventricular Hypertrophy

HYZAAR is indicated to reduce the risk of stroke in patients with hypertension and left ventricular hypertrophy, but there is evidence that this benefit does not apply to Black patients. [See Use in Specific Populations (8.6), Clinical Pharmacology (12.3), and Dosage and Administration (2.2).]

2 DOSAGE AND ADMINISTRATION

2.1 Hypertension

The usual starting dose of HYZAAR is 50/12.5 (losartan 50 mg/hydrochlorothiazide 12.5 mg) once daily. The dosage can be increased after 3 weeks of therapy to a maximum of 100/25 (losartan 100 mg/hydrochlorothiazide 25 mg) once daily as needed to control blood pressure [see Clinical Studies (14.2)].

Initiate a patient whose blood pressure is not adequately controlled with losartan 50 mg monotherapy with HYZAAR 50/12.5 once daily. If blood pressure remains uncontrolled after about 3 weeks of therapy, the dosage may be increased to two tablets of HYZAAR 50/12.5 once daily or one tablet of HYZAAR 100/25 once daily.

Initiate a patient whose blood pressure is not adequately controlled with losartan 100 mg monotherapy with HYZAAR 100/12.5 (losartan 100 mg/hydrochlorothiazide 12.5 mg) once daily. If blood pressure remains uncontrolled after about 3 weeks of therapy, increase the dose to two tablets of HYZAAR 50/12.5 once daily or one tablet of HYZAAR 100/25 once daily.

Initiate a patient whose blood pressure is inadequately controlled with hydrochlorothiazide 25 mg once daily, or is controlled but who experiences hypokalemia with this regimen, on HYZAAR 50/12.5 once daily, reducing the dose of hydrochlorothiazide without reducing the overall expected antihypertensive response. Evaluate the clinical response to HYZAAR 50/12.5 and, if blood pressure remains uncontrolled after about 3 weeks of therapy, increase the dose to two tablets of HYZAAR 50/12.5 once daily or one tablet of HYZAAR 100/25 once daily.

2.2 Hypertensive Patients with Left Ventricular Hypertrophy

In patients whose blood pressure is not adequately controlled on 50 mg losartan potassium, initiate treatment with HYZAAR 50/12.5. If additional blood pressure reduction is needed, increase the dose to HYZAAR 100/12.5, followed by HYZAAR 100/25. For further blood pressure reduction add other antihypertensives [see Clinical Studies (14)].

3 DOSAGE FORMS AND STRENGTHS

- HYZAAR 50/12.5 are yellow, oval, film-coated tablets, with code 717 on one side.
- HYZAAR 100/12.5 are white, oval, film-coated tablets, with code 745 on one side.
- HYZAAR 100/25 are light yellow, oval, film-coated tablets, with code 747 on one side.

4 CONTRAINDICATIONS

HYZAAR is contraindicated:

- In patients who are hypersensitive to any component of this product.
- In patients with anuria
- For coadministration with aliskiren in patients with diabetes

5 WARNINGS AND PRECAUTIONS

5.1 Fetal Toxicity

HYZAAR can cause fetal harm when administered to a pregnant woman. Use of drugs that act on the renin-angiotensin system during the second and third trimesters of pregnancy reduces fetal renal function and increases fetal and neonatal morbidity and death. Resulting oligohydramnios can be associated with fetal lung hypoplasia and skeletal deformations. Potential neonatal adverse effects include skull hypoplasia, anuria, hypotension, renal failure, and death. When pregnancy is detected, discontinue HYZAAR as soon as possible.

Thiazides cross the placental barrier and appear in cord blood. Adverse reactions include fetal or neonatal jaundice, thrombocytopenia [see Use in Specific Populations (8.1)].

5.2 Hypotension in Volume- or Salt-Depleted Patients

In patients with an activated renin-angiotensin system, such as volume- or salt-depleted patients (e.g., those being treated with high doses of diuretics), symptomatic hypotension may occur after initiation of treatment with HYZAAR. Correct volume or salt depletion prior to administration of HYZAAR. Do not use HYZAAR as initial therapy in patients with intravascular volume depletion.

5.3 Impaired Renal Function

Changes in renal function including acute renal failure can be caused by drugs that inhibit the renin-angiotensin system and by diuretics. Patients whose renal function may depend in part on the activity of the renin-angiotensin system (e.g., patients with renal artery stenosis, chronic kidney disease, severe congestive heart failure, or volume depletion) may be at particular risk of developing acute renal failure on HYZAAR. Monitor renal function periodically in these patients. Consider withholding or discontinuing therapy in patients who develop a clinically significant decrease in renal function on HYZAAR [see Drug Interactions (7.3) and Use in Specific Populations (8.8)].

5.4 Hypersensitivity

Hypersensitivity reactions to hydrochlorothiazide may occur in patients with or without a history of allergy or bronchial asthma but are more likely in patients with such a history [see Adverse Reactions (6.2)].

5.5 Electrolyte and Metabolic Effects

In double-blind clinical trials of various doses of losartan potassium and hydrochlorothiazide, the incidence of hypertensive patients who developed hypokalemia (serum potassium <3.5 mEq/L) was 6.7% versus 3.5% for placebo; the incidence of hyperkalemia (serum potassium >5.7 mEq/L) was 0.4% versus 0% for placebo.

HYZAAR contains hydrochlorothiazide which can cause hypokalemia, hyponatremia and hypomagnesemia. Hypomagnesemia can result in hypokalemia which may be difficult to treat despite potassium repletion. HYZAAR also contains losartan which can cause hyperkalemia. Monitor serum electrolytes periodically [see Drug Interactions (7.1)].

Concomitant use of other drugs that may increase serum potassium may lead to hyperkalemia [see Drug Interactions (7.1)].

Hydrochlorothiazide may alter glucose tolerance and raise serum levels of cholesterol and triglycerides.

Hyperuricemia may occur or frank gout may be precipitated in patients receiving thiazide therapy. Because losartan decreases uric acid, losartan in combination with hydrochlorothiazide attenuates the diuretic-induced hyperuricemia.

Hydrochlorothiazide decreases urinary calcium excretion and may cause elevations of serum calcium. Monitor calcium levels.

5.6 Acute Myopia and Secondary Angle-Closure Glaucoma

Hydrochlorothiazide, a sulfonamide, can cause an idiosyncratic reaction, resulting in acute transient myopia and acute angle-closure glaucoma. Symptoms include acute onset of decreased visual acuity or ocular pain and typically occur within hours to weeks of drug initiation. Untreated acute angle-closure glaucoma can lead to permanent vision loss. The primary treatment is to discontinue hydrochlorothiazide as rapidly as possible. Prompt medical or surgical treatments may need to be considered if the intraocular pressure remains uncontrolled. Risk factors for developing acute angle-closure glaucoma may include a history of sulfonamide or penicillin allergy.

5.7 Systemic Lupus Erythematosus

Thiazide diuretics have been reported to cause exacerbation or activation of systemic lupus erythematosus.

6 ADVERSE REACTIONS

6.1 Clinical Trials Experience

Because clinical trials are conducted under widely varying conditions, adverse reaction rates observed in the clinical trials of a drug cannot be directly compared to rates in the clinical trials of another drug and may not reflect the rates observed in practice.

Losartan potassium-hydrochlorothiazide has been evaluated for safety in 858 patients treated for essential hypertension and 3889 patients treated for hypertension and left ventricular hypertrophy. Most adverse reactions have been mild and transient in nature and have not required discontinuation of therapy. In controlled clinical trials, discontinuation of therapy due to clinical adverse events was required in only 2.8% and 2.3% of patients treated with the combination and placebo, respectively.

In these double-blind controlled clinical trials, adverse reactions occurring in greater than 2% of subjects treated with losartan-hydrochlorothiazide and at a greater rate than placebo were: back pain (2.1% vs 0.6%), dizziness (5.7% vs 2.9%), and upper respiratory infection (6.1% vs 4.6%).

The following additional adverse reactions have been reported in clinical trials with HYZAAR and/or the individual components:

Blood and the lymphatic system disorders: Anemia, aplastic anemia, hemolytic anemia, leukopenia, agranulocytosis.

Metabolism and nutrition disorders: Anorexia, hyperglycemia, hyperuricemia, electrolyte imbalance including hyponatremia and hypokalemia.

Psychiatric disorders: Insomnia, restlessness.

Nervous system disorders: Dysgeusia, headache, migraine, paraesthesias.

Eye disorders: Xanthopsia, transient blurred vision.

Cardiac disorders: Palpitation, tachycardia.

Vascular disorders: Dose-related orthostatic effects, necrotizing angiitis (vasculitis, cutaneous vasculitis).

Respiratory, thoracic and mediastinal disorders: Nasal congestion.

Gastrointestinal disorders: Dyspepsia, abdominal pain, gastric irritation, cramping, nausea, vomiting, pancreatitis, sialoadenitis.

Hepato-biliary disorders: Jaundice (intrahepatic cholestatic jaundice).

Skin and subcutaneous tissue disorders: Rash, pruritus, purpura, toxic epidermal necrolysis, urticaria, photosensitivity, cutaneous lupus erythematosus.

Musculoskeletal and connective tissue disorders: Muscle cramps, muscle spasm.

Renal and urinary disorders: Glycosuria, renal dysfunction, interstitial nephritis, renal failure.

Reproductive system and breast disorders: Erectile dysfunction/impotence.

General disorders and administration site conditions: Chest pain, malaise, weakness.

Investigations: Liver function abnormalities.

Cough

Persistent dry cough has been associated with ACE-inhibitor use and in practice can be a cause of discontinuation of ACE-inhibitor therapy. Two prospective, parallel-group, double-blind, randomized, controlled trials were conducted to assess the effects of losartan on the incidence of cough in hypertensive patients who had experienced cough while receiving ACE-inhibitor therapy. Patients who had typical ACE-inhibitor cough when challenged with lisinopril, whose cough disappeared on placebo, were randomized to losartan 50 mg, lisinopril 20 mg, or either placebo (one study, n=97) or 25 mg hydrochlorothiazide (n=135). The double-blind treatment period lasted up to 8 weeks. The incidence of cough is shown in Table 1 below.

Table 1:
Study 1 [Demographics = (89% Caucasian, 64% female)] | HCTZ | Losartan | Lisinopril
Cough | 25% | 17% | 69%
Study 2 [Demographics = (90% Caucasian, 51% female)] | Placebo | Losartan | Lisinopril
Cough | 35% | 29% | 62%

These studies demonstrate that the incidence of cough associated with losartan therapy, in a population that all had cough associated with ACE-inhibitor therapy, is similar to that associated with hydrochlorothiazide or placebo therapy.

Cases of cough, including positive re-challenges, have been reported with the use of losartan in postmarketing experience.

6.2 Postmarketing Experience

The following adverse reactions have been identified during post-approval use of HYZAAR. Because these reactions are reported voluntarily from a population of uncertain size, it is not always possible to estimate their frequency reliably or to establish a causal relationship to drug exposure.

Digestive: Hepatitis has been reported rarely in patients treated with losartan.

Hematologic: Thrombocytopenia.

Hypersensitivity: Angioedema, including swelling of the larynx and glottis, causing airway obstruction and/or swelling of the face, lips, pharynx, tongue, and/or swelling of the intestine. Vasculitis, including Henoch-Schönlein purpura; anaphylactic reactions which can present as respiratory distress (including pneumonitis and pulmonary edema).

Musculoskeletal: Rhabdomyolysis.

Skin: Erythroderma.

Non-melanoma Skin Cancer: Hydrochlorothiazide is associated with an increased risk of non-melanoma skin cancer. In a study conducted in the Sentinel System, increased risk was predominantly for squamous cell carcinoma (SCC) and in white patients taking large cumulative doses. The increased risk for SCC in the overall population was approximately 1 additional case per 16,000 patients per year, and for white patients taking a cumulative dose of ≥50,000mg the risk increase was approximately 1 additional SCC case for every 6,700 patients per year.

7 DRUG INTERACTIONS

7.1 Agents Increasing Serum Potassium

Coadministration of losartan with other drugs that raise serum potassium levels may result in hyperkalemia. Monitor serum potassium in such patients.

7.2 Lithium

Increases in serum lithium concentrations and lithium toxicity have been reported with concomitant use of angiotensin II receptor antagonists or thiazide diuretics. Monitor lithium levels in patients receiving HYZAAR and lithium.

7.3 Non-Steroidal Anti-Inflammatory Agents Including Selective Cyclooxygenase-2 Inhibitors

Losartan Potassium

In patients who are elderly, volume-depleted (including those on diuretic therapy), or with compromised renal function, coadministration of NSAIDs, including selective COX-2 inhibitors, with angiotensin II receptor antagonists (including losartan) may result in deterioration of renal function, including possible acute renal failure. These effects are usually reversible. Monitor renal function periodically in patients receiving losartan and NSAID therapy.

The antihypertensive effect of angiotensin II receptor antagonists, including losartan, may be attenuated by NSAIDs, including selective COX-2 inhibitors.

Hydrochlorothiazide

The administration of a non-steroidal anti-inflammatory agent including a selective COX-2 inhibitor can reduce the diuretic, natriuretic, and antihypertensive effects of loop, potassium-sparing and thiazide diuretics. Therefore, when HYZAAR and non-steroidal anti-inflammatory agents including selective COX-2 inhibitors are used concomitantly, observe closely to determine if the desired effect of the diuretic is obtained.

In patients receiving diuretic therapy, coadministration of NSAIDs with angiotensin receptor blockers, including losartan, may result in deterioration of renal function, including possible acute renal failure. These effects are usually reversible. Monitor renal function periodically in patients receiving hydrochlorothiazide, losartan, and NSAID therapy.

7.4 Dual Blockade of the Renin-Angiotensin System (RAS)

Dual blockade of the RAS with angiotensin receptor blockers, ACE inhibitors, or aliskiren is associated with increased risks of hypotension, syncope, hyperkalemia, and changes in renal function (including acute renal failure) compared to monotherapy.

The Veterans Affairs Nephropathy in Diabetes (VA NEPHRON-D) trial enrolled 1448 patients with type 2 diabetes, elevated urinary-albumin-to-creatinine ratio, and decreased estimated glomerular filtration rate (GFR 30 to 89.9 mL/min), randomized them to lisinopril or placebo on a background of losartan therapy and followed them for a median of 2.2 years. Patients receiving the combination of losartan and lisinopril did not obtain any additional benefit compared to monotherapy for the combined endpoint of decline in GFR, end-stage renal disease, or death, but experienced an increased incidence of hyperkalemia and acute kidney injury compared with the monotherapy group.

Closely monitor blood pressure, renal function, and electrolytes in patients on HYZAAR and other agents that affect the RAS.

Do not coadminister aliskiren with HYZAAR in patients with diabetes. Avoid use of aliskiren with HYZAAR in patients with renal impairment (GFR <60 mL/min).

7.5 The Use of Hydrochlorothiazide with Other Drugs

When administered concurrently, the following drugs may interact with thiazide diuretics [see Clinical Pharmacology (12.3)]:

Antidiabetic drugs (oral agents and insulin) — dosage adjustment of the antidiabetic drug may be required.

Cholestyramine and colestipol resins — Absorption of hydrochlorothiazide is impaired in the presence of anionic exchange resins. Single doses of either cholestyramine or colestipol resins bind the hydrochlorothiazide and reduce its absorption from the gastrointestinal tract by up to 85 and 43 percent, respectively. Stagger the dosage of hydrochlorothiazide and the resin such that hydrochlorothiazide is administered at least 4 hours before or 4 to 6 hours after the administration of the resin.

8 USE IN SPECIFIC POPULATIONS

8.1 Pregnancy

Risk Summary

HYZAAR can cause fetal harm when administered to a pregnant woman. Use of drugs that act on the renin-angiotensin system during the second and third trimesters of pregnancy reduces fetal renal function and increases fetal and neonatal morbidity and death. Most epidemiologic studies examining fetal abnormalities after exposure to antihypertensive use in the first trimester have not distinguished drugs affecting the renin-angiotensin system from other antihypertensive agents. When pregnancy is detected, discontinue HYZAAR as soon as possible (see Clinical Considerations).

The estimated background risk of major birth defects and miscarriage for the indicated population is unknown. All pregnancies have a background risk of birth defect, loss, or other adverse outcomes. In the U.S. general population, the estimated background risk of major birth defects and miscarriage in clinically recognized pregnancies is 2% to 4% and 15% to 20%, respectively.

Clinical Considerations

Disease-associated Maternal and/or Embryo/Fetal Risk

Hypertension in pregnancy increases the maternal risk for pre-eclampsia, gestational diabetes, premature delivery, and delivery complications (e.g., need for cesarean section, post-partum hemorrhage). Hypertension increases the fetal risk for intrauterine growth restriction and intrauterine death. Pregnant women with hypertension should be carefully monitored and managed accordingly.

Fetal/Neonatal Adverse Reactions

Losartan:

Use of drugs that act on the renin-angiotensin system in the second and third trimesters of pregnancy can result in the following: oligohydramnios, reduced fetal renal function leading to anuria and renal failure, fetal lung hypoplasia, skeletal deformations, including skull hypoplasia, hypotension, and death.

In the unusual case that there is no appropriate alternative to therapy with drugs affecting the renin-angiotensin system for a particular patient, apprise the mother of the potential risk to the fetus. Perform serial ultrasound examinations to assess the intra-amniotic environment. If oligohydramnios is observed, discontinue HYZAAR, unless it is considered lifesaving for the mother. Fetal testing may be appropriate, based on the week of gestation. Patients and physicians should be aware, however, that oligohydramnios may not appear until after the fetus has sustained irreversible injury. Closely observe neonates with histories of in utero exposure to HYZAAR for hypotension, oliguria, and hyperkalemia. In neonates with a history of in utero exposure to HYZAAR, if oliguria or hypotension occurs, support blood pressure and renal perfusion. Exchange transfusions or dialysis may be required as a means of reversing hypotension and replacing renal function.

Hydrochlorothiazide:

Thiazides can cross the placenta, and concentrations reached in the umbilical vein approach those in the maternal plasma. Hydrochlorothiazide, like other diuretics, can cause placental hypoperfusion. It accumulates in the amniotic fluid, with reported concentrations up to 19 times higher than in umbilical vein plasma. Use of thiazides during pregnancy is associated with a risk of fetal or neonatal jaundice or thrombocytopenia. Since they do not alter the course of pre-eclampsia, these drugs should not be used to treat hypertension in pregnant women. The use of hydrochlorothiazide for other indications in pregnancy should be avoided.

Data

Animal Data

There was no evidence of teratogenicity in rats or rabbits treated with a maximum losartan potassium dose of 10 mg/kg/day in combination with 2.5 mg/kg/day of hydrochlorothiazide. At these dosages, respective exposures (AUCs) of losartan, its active metabolite, and hydrochlorothiazide in rabbits were approximately 5, 1.5, and 1.0 times those achieved in humans with 100 mg losartan in combination with 25 mg hydrochlorothiazide. AUC values for losartan, its active metabolite and hydrochlorothiazide, extrapolated from data obtained with losartan administered to rats at a dose of 50 mg/kg/day in combination with 12.5 mg/kg/day of hydrochlorothiazide, were approximately 6, 2, and 2 times greater than those achieved in humans with 100 mg of losartan in combination with 25 mg of hydrochlorothiazide. Fetal toxicity in rats, as evidenced by a slight increase in supernumerary ribs, was observed when females were treated prior to and throughout gestation with 10 mg/kg/day losartan in combination with 2.5 mg/kg/day hydrochlorothiazide. As also observed in studies with losartan alone, adverse fetal and neonatal effects, including decreased body weight, renal toxicity, and mortality, occurred when pregnant rats were treated during late gestation and/or lactation with 50 mg/kg/day losartan in combination with 12.5 mg/kg/day hydrochlorothiazide. Respective AUCs for losartan, its active metabolite and hydrochlorothiazide at these dosages in rats were approximately 35, 10 and 10 times greater than those achieved in humans with the administration of 100 mg of losartan in combination with 25 mg hydrochlorothiazide. When hydrochlorothiazide was administered without losartan to pregnant mice and rats during their respective periods of major organogenesis, at doses up to 3000 and 1000 mg/kg/day, respectively, there was no evidence of harm to the fetus.

8.2 Lactation

Risk Summary

It is not known whether losartan is excreted in human milk, but significant levels of losartan and its active metabolite were shown to be present in rat milk. Thiazides appear in human milk. Because of the potential for adverse effects on the nursing infant, a decision should be made whether to discontinue nursing or discontinue the drug, taking into account the importance of the drug to the mother.

8.4 Pediatric Use

Safety and effectiveness of HYZAAR in pediatric patients have not been established.

Neonates with a history of in utero exposure to HYZAAR: If oliguria or hypotension occurs, direct attention toward support of blood pressure and renal perfusion. Exchange transfusion or dialysis may be required as means of reversing hypotension and/or substituting for disordered renal function.

8.5 Geriatric Use

In a controlled clinical study for the reduction in the combined risk of cardiovascular death, stroke and myocardial infarction in hypertensive patients with left ventricular hypertrophy, 2857 patients (62%) were 65 years and over, while 808 patients (18%) were 75 years and over. In an effort to control blood pressure in this study, patients were coadministered losartan and hydrochlorothiazide 74% of the total time they were on study drug. No overall differences in effectiveness were observed between these patients and younger patients. Adverse events were somewhat more frequent in the elderly compared to non-elderly patients for both the losartan-hydrochlorothiazide and the control groups [see Clinical Pharmacology (12.3)].

8.6 Race

In the Losartan Intervention For Endpoint reduction in hypertension (LIFE) study, Black patients with hypertension and left ventricular hypertrophy treated with atenolol had a lower risk of stroke, the primary composite endpoint, as compared with Black patients treated with losartan (both cotreated with hydrochlorothiazide in the majority of patients). In the subgroup of Black patients (n=533, 6% of the LIFE study patients), there were 29 primary endpoints among 263 patients on atenolol (11%, 26 per 1000 patient-years) and 46 primary endpoints among 270 patients (17%, 42 per 1000 patient-years) on losartan. This finding could not be explained on the basis of differences in the populations other than race or on any imbalances between treatment groups. In addition, blood pressure reductions in both treatment groups were consistent between Black and non-Black patients. Given the difficulty in interpreting subset differences in large trials, it cannot be known whether the observed difference is the result of chance. However, the LIFE study provides no evidence that the benefits of losartan on reducing the risk of cardiovascular events in hypertensive patients with left ventricular hypertrophy apply to Black patients [see Clinical Pharmacology (12.3)].

8.7 Hepatic Impairment

Initiation of HYZAAR is not recommended for patients with hepatic impairment because the appropriate starting dose of losartan, 25 mg, is not available.

8.8 Renal Impairment

Changes in renal function have been reported in susceptible individuals [see Dosage and Administration (2.1), Warnings and Precautions (5.4), and Clinical Pharmacology (12.3)]. Safety and effectiveness of HYZAAR in patients with severe renal impairment (creatinine clearance <30 mL/min) have not been established.

10 OVERDOSAGE

Losartan Potassium

Significant lethality was observed in mice and rats after oral administration of 1000 mg/kg and 2000 mg/kg, respectively, about 44 and 170 times the maximum recommended human dose on a mg/m^2 basis.

Limited data are available in regard to overdosage in humans. The most likely manifestation of overdosage would be hypotension and tachycardia; bradycardia could occur from parasympathetic (vagal) stimulation. If symptomatic hypotension should occur, supportive treatment should be instituted.

Neither losartan nor its active metabolite can be removed by hemodialysis.

Hydrochlorothiazide

The oral LD50 of hydrochlorothiazide is greater than 10 g/kg in both mice and rats. The most common signs and symptoms observed are those caused by electrolyte depletion (hypokalemia, hypochloremia, hyponatremia) and dehydration resulting from excessive diuresis. If digitalis has also been administered, hypokalemia may accentuate cardiac arrhythmias. The degree to which hydrochlorothiazide is removed by hemodialysis has not been established.

11 DESCRIPTION

HYZAAR 50/12.5 (losartan potassium-hydrochlorothiazide), HYZAAR 100/12.5 (losartan potassium-hydrochlorothiazide) and HYZAAR 100/25 (losartan potassium-hydrochlorothiazide) tablets combine an angiotensin II receptor blocker acting on the AT1 receptor subtype and a diuretic, hydrochlorothiazide.

Losartan potassium, a non-peptide molecule, is chemically described as 2-butyl-4-chloro-1-[p-(o-1H-tetrazol-5-ylphenyl)benzyl]imidazole-5-methanol monopotassium salt. Its empirical formula is C22H22ClKN6O, and its structural formula is:

Losartan potassium is a white to off-white free-flowing crystalline powder with a molecular weight of 461.01. It is freely soluble in water, soluble in alcohols, and slightly soluble in common organic solvents, such as acetonitrile and methyl ethyl ketone.

Oxidation of the 5-hydroxymethyl group on the imidazole ring results in the active metabolite of losartan.

Hydrochlorothiazide is 6-chloro-3,4-dihydro-2H-1,2,4-benzothiadiazine-7-sulfonamide 1,1-dioxide. Its empirical formula is C7H8ClN3O4S2 and its structural formula is:

Hydrochlorothiazide is a white, or practically white, crystalline powder with a molecular weight of 297.74, which is slightly soluble in water, but freely soluble in sodium hydroxide solution.

HYZAAR is available for oral administration in three tablet combinations of losartan and hydrochlorothiazide. HYZAAR 50/12.5 contains 50 mg of losartan potassium and 12.5 mg of hydrochlorothiazide. HYZAAR 100/12.5 contains 100 mg of losartan potassium and 12.5 mg of hydrochlorothiazide. HYZAAR 100/25 contains 100 mg of losartan potassium and 25 mg of hydrochlorothiazide. Inactive ingredients are microcrystalline cellulose, lactose hydrous, pregelatinized starch, magnesium stearate, hydroxypropyl cellulose, hypromellose, and titanium dioxide. HYZAAR 50/12.5 and HYZAAR 100/25 also contain D&C yellow No. 10 aluminum lake. HYZAAR 50/12.5, HYZAAR 100/12.5, and HYZAAR 100/25 may also contain carnauba wax.

HYZAAR 50/12.5 contains 4.24 mg (0.108 mEq) of potassium, HYZAAR 100/12.5 contains 8.48 mg (0.216 mEq) of potassium, and HYZAAR 100/25 contains 8.48 mg (0.216 mEq) of potassium.

12 CLINICAL PHARMACOLOGY

12.1 Mechanism of Action

Losartan Potassium

Angiotensin II [formed from angiotensin I in a reaction catalyzed by angiotensin converting enzyme (ACE, kininase II)], is a potent vasoconstrictor, the primary vasoactive hormone of the renin-angiotensin system and an important component in the pathophysiology of hypertension. It also stimulates aldosterone secretion by the adrenal cortex. Losartan and its principal active metabolite block the vasoconstrictor and aldosterone-secreting effects of angiotensin II by selectively blocking the binding of angiotensin II to the AT1 receptor found in many tissues (e.g., vascular smooth muscle, adrenal gland). There is also an AT2 receptor found in many tissues but it is not known to be associated with cardiovascular homeostasis. Neither losartan nor its principal active metabolite exhibits any partial agonist activity at the AT1 receptor, and both have much greater affinity (about 1000-fold) for the AT1 receptor than for the AT2 receptor. In vitro binding studies indicate that losartan is a reversible, competitive inhibitor of the AT1 receptor. The active metabolite is 10 to 40 times more potent by weight than losartan and appears to be a reversible, non-competitive inhibitor of the AT1 receptor.

Neither losartan nor its active metabolite inhibits ACE (kininase II, the enzyme that converts angiotensin I to angiotensin II and degrades bradykinin), nor do they bind to or block other hormone receptors or ion channels known to be important in cardiovascular regulation.

Hydrochlorothiazide

Hydrochlorothiazide is a thiazide diuretic. Thiazides affect the renal tubular mechanisms of electrolyte reabsorption, directly increasing excretion of sodium and chloride in approximately equivalent amounts. Indirectly, the diuretic action of hydrochlorothiazide reduces plasma volume, with consequent increases in plasma renin activity, increases in aldosterone secretion, increases in urinary potassium loss, and decreases in serum potassium. The renin-aldosterone link is mediated by angiotensin II, so coadministration of an angiotensin II receptor antagonist tends to reverse the potassium loss associated with these diuretics. The mechanism of the antihypertensive effect of thiazides is unknown.

12.2 Pharmacodynamics

Losartan Potassium

Losartan inhibits the pressor effect of angiotensin II (as well as angiotensin I) infusions. A dose of 100 mg inhibits the pressor effect by about 85% at peak with 25-40% inhibition persisting for 24 hours. Removal of the negative feedback of angiotensin II causes a doubling to tripling in plasma renin activity and consequent rise in angiotensin II plasma concentration in hypertensive patients. Losartan does not affect the response to bradykinin, whereas ACE inhibitors increase the response to bradykinin. Aldosterone plasma concentrations fall following losartan administration. In spite of the effect of losartan on aldosterone secretion, very little effect on serum potassium was observed.

The effect of losartan is substantially present within one week but in some studies the maximal effect occurred in 3-6 weeks. In long-term follow-up studies (without placebo control) the effect of losartan appeared to be maintained for up to a year. There is no apparent rebound effect after abrupt withdrawal of losartan. There was essentially no change in average heart rate in losartan-treated patients in controlled trials.

Hydrochlorothiazide

After oral administration of hydrochlorothiazide, diuresis begins within 2 hours, peaks in about 4 hours, and lasts about 6 to 12 hours.

Drug Interactions

Hydrochlorothiazide

Alcohol, barbiturates, or narcotics — potentiation of orthostatic hypotension may occur.

Other antihypertensive drugs — additive effect or potentiation.

Skeletal muscle relaxants, nondepolarizing (e.g., tubocurarine) — possible increased responsiveness to the muscle relaxant.

Corticosteroids, ACTH, or glycyrrhizin (found in liquorice) — intensified electrolyte depletion, particularly hypokalemia.

Pressor amines (e.g., norepinephrine) — possible decreased response to pressor amines but not sufficient to preclude their use.

12.3 Pharmacokinetics

Losartan Potassium

Absorption: Following oral administration, losartan is well absorbed and undergoes substantial first-pass metabolism. The systemic bioavailability of losartan is approximately 33%. Mean peak concentrations of losartan and its active metabolite are reached in 1 hour and in 3-4 hours, respectively. While maximum plasma concentrations of losartan and its active metabolite are approximately equal, the AUC (area under the curve) of the metabolite is about 4 times as great as that of losartan. A meal slows absorption of losartan and decreases its Cmax but has only minor effects on losartan AUC or on the AUC of the metabolite (~10% decrease). The pharmacokinetics of losartan and its active metabolite are linear with oral losartan doses up to 200 mg and do not change over time.

Distribution: The volume of distribution of losartan and the active metabolite is about 34 liters and 12 liters, respectively. Both losartan and its active metabolite are highly bound to plasma proteins, primarily albumin, with plasma free fractions of 1.3% and 0.2%, respectively. Plasma protein binding is constant over the concentration range achieved with recommended doses. Studies in rats indicate that losartan crosses the blood-brain barrier poorly, if at all.

Metabolism: Losartan is an orally active agent that undergoes substantial first-pass metabolism by cytochrome P450 enzymes. It is converted, in part, to an active carboxylic acid metabolite that is responsible for most of the angiotensin II receptor antagonism that follows losartan treatment. About 14% of an orally-administered dose of losartan is converted to the active metabolite. In addition to the active carboxylic acid metabolite, several inactive metabolites are formed. In vitro studies indicate that cytochrome P450 2C9 and 3A4 are involved in the biotransformation of losartan to its metabolites.

Elimination: Total plasma clearance of losartan and the active metabolite is about 600 mL/min and 50 mL/min, respectively, with renal clearance of about 75 mL/min and 25 mL/min, respectively. The terminal half-life of losartan is about 2 hours and of the metabolite is about 6-9 hours. After single doses of losartan administered orally, about 4% of the dose is excreted unchanged in the urine and about 6% is excreted in urine as active metabolite. Biliary excretion contributes to the elimination of losartan and its metabolites. Following oral ^14C-labeled losartan, about 35% of radioactivity is recovered in the urine and about 60% in the feces. Following an intravenous dose of ^14C-labeled losartan, about 45% of radioactivity is recovered in the urine and 50% in the feces. Neither losartan nor its metabolite accumulate in plasma upon repeated once-daily dosing.

Hydrochlorothiazide

Hydrochlorothiazide is not metabolized but is eliminated rapidly by the kidney. When plasma levels have been followed for at least 24 hours, the plasma half-life has been observed to vary between 5.6 and 14.8 hours. At least 61 percent of the oral dose is eliminated unchanged within 24 hours. Hydrochlorothiazide crosses the placental but not the blood-brain barrier and is excreted in breast milk.

Specific Populations

Geriatric and Gender

Losartan pharmacokinetics have been investigated in the elderly (65-75 years) and in both genders. Plasma concentrations of losartan and its active metabolite are similar in elderly and young hypertensives. Plasma concentrations of losartan were about twice as high in female hypertensives as male hypertensives, but concentrations of the active metabolite were similar in males and females.

Race

Pharmacokinetic differences due to race have not been studied [see also Use in Specific Populations (8.6)].

Hepatic Insufficiency

Following oral administration in patients with mild to moderate alcoholic cirrhosis of the liver, plasma concentrations of losartan and its active metabolite were, respectively, 5 times and about 1.7 times those in young male volunteers. Compared to normal subjects, the total plasma clearance of losartan in patients with hepatic insufficiency was about 50% lower, and the oral bioavailability was about doubled. The lower starting dose of losartan recommended for use in patients with hepatic impairment cannot be given using HYZAAR. Its use in such patients as a means of losartan titration is, therefore, not recommended [see Warnings and Precautions (5.3) and Use in Specific Populations (8.7)].

Renal Insufficiency

Losartan

Following oral administration, plasma concentrations and AUCs of losartan and its active metabolite are increased by 50-90% in patients with mild (creatinine clearance of 50 to 74 mL/min) or moderate (creatinine clearance 30 to 49 mL/min) renal insufficiency. In this study, renal clearance was reduced by 55-85% for both losartan and its active metabolite in patients with mild or moderate renal insufficiency. Neither losartan nor its active metabolite can be removed by hemodialysis.

Hydrochlorothiazide

Following oral administration, the AUC for hydrochlorothiazide is increased by 70 and 700% for patients with mild and moderate renal insufficiency, respectively. In this study, renal clearance of hydrochlorothiazide decreased by 45 and 85% in patients with mild and moderate renal impairment, respectively.

Use the usual regimens of therapy with HYZAAR as long as the patient's creatinine clearance is greater than 30 mL/min. Safety and effectiveness of HYZAAR in patients with severe renal impairment (creatinine clearance less than 30 mL/min) have not been established [see Use in Specific Populations (8.8)].

Drug Interactions

Losartan Potassium

No clinically significant drug interactions have been found in studies of losartan potassium with hydrochlorothiazide, digoxin, warfarin, cimetidine and phenobarbital. However, rifampin has been shown to decrease the AUC of losartan and its active metabolite by 30% and 40%, respectively. Fluconazole, an inhibitor of cytochrome P450 2C9, decreased the AUC of the active metabolite by approximately 40%, but increased the AUC of losartan by approximately 70% following multiple doses. Conversion of losartan to its active metabolite after intravenous administration is not affected by ketoconazole, an inhibitor of P450 3A4.The AUC of active metabolite following oral losartan was not affected by erythromycin, an inhibitor of P450 3A4, but the AUC of losartan was increased by 30%.

The pharmacodynamic consequences of concomitant use of losartan and inhibitors of P450 2C9 have not been examined. Subjects who do not metabolize losartan to active metabolite have been shown to have a specific, rare defect in cytochrome P450 2C9. These data suggest that the conversion of losartan to its active metabolite is mediated primarily by P450 2C9 and not P450 3A4.

13 NONCLINICAL TOXICOLOGY

13.1 Carcinogenesis, Mutagenesis, Impairment of Fertility

Losartan Potassium-Hydrochlorothiazide

No carcinogenicity studies have been conducted with the losartan potassium-hydrochlorothiazide combination.

Losartan potassium-hydrochlorothiazide when tested at a weight ratio of 4:1, was negative in the Ames microbial mutagenesis assay and the V-79 Chinese hamster lung cell mutagenesis assay. In addition, there was no evidence of direct genotoxicity in the in vitro alkaline elution assay in rat hepatocytes and in vitro chromosomal aberration assay in Chinese hamster ovary cells at noncytotoxic concentrations.

Losartan potassium, coadministered with hydrochlorothiazide, had no effect on the fertility or mating behavior of male rats at dosages up to 135 mg/kg/day of losartan and 33.75 mg/kg/day of hydrochlorothiazide. These dosages have been shown to provide respective systemic exposures (AUCs) for losartan, its active metabolite and hydrochlorothiazide that are approximately 60, 60 and 30 times greater than those achieved in humans with 100 mg of losartan potassium in combination with 25 mg of hydrochlorothiazide. In female rats, however, the coadministration of doses as low as 10 mg/kg/day of losartan and 2.5 mg/kg/day of hydrochlorothiazide was associated with slight but statistically significant decreases in fecundity and fertility indices. AUC values for losartan, its active metabolite and hydrochlorothiazide, extrapolated from data obtained with losartan administered to rats at a dose of 50 mg/kg/day in combination with 12.5 mg/kg/day of hydrochlorothiazide, were approximately 6, 2, and 2 times greater than those achieved in humans with 100 mg of losartan in combination with 25 mg of hydrochlorothiazide.

Losartan Potassium

Losartan potassium was not carcinogenic when administered at maximally tolerated dosages to rats and mice for 105 and 92 weeks, respectively. Female rats given the highest dose (270 mg/kg/day) had a slightly higher incidence of pancreatic acinar adenoma. The maximally tolerated dosages (270 mg/kg/day in rats, 200 mg/kg/day in mice) provided systemic exposures for losartan and its pharmacologically active metabolite that were approximately 160 and 90 times (rats) and 30 and 15 times (mice) the exposure of a 50 kg human given 100 mg per day.

Losartan potassium was negative in the microbial mutagenesis and V-79 mammalian cell mutagenesis assays and in the in vitro alkaline elution and in vitro and in vivo chromosomal aberration assays. In addition, the active metabolite showed no evidence of genotoxicity in the microbial mutagenesis, in vitro alkaline elution, and in vitro chromosomal aberration assays.

Fertility and reproductive performance were not affected in studies with male rats given oral doses of losartan potassium up to approximately 150 mg/kg/day. The administration of toxic dosage levels in females (300/200 mg/kg/day) was associated with a significant (p<0.05) decrease in the number of corpora lutea/female, implants/female, and live fetuses/female at C-section. At 100 mg/kg/day only a decrease in the number of corpora lutea/female was observed. The relationship of these findings to drug-treatment is uncertain since there was no effect at these dosage levels on implants/pregnant female, percent post-implantation loss, or live animals/litter at parturition. In nonpregnant rats dosed at 135 mg/kg/day for 7 days, systemic exposure (AUCs) for losartan and its active metabolite were approximately 66 and 26 times the exposure achieved in man at the maximum recommended human daily dosage (100 mg).

Hydrochlorothiazide

Two-year feeding studies in mice and rats conducted under the auspices of the National Toxicology Program (NTP) uncovered no evidence of a carcinogenic potential of hydrochlorothiazide in female mice (at doses of up to approximately 600 mg/kg/day) or in male and female rats (at doses of up to approximately 100 mg/kg/day). The NTP, however, found equivocal evidence for hepatocarcinogenicity in male mice.

Hydrochlorothiazide was not genotoxic in vitro in the Ames mutagenicity assay of Salmonella typhimurium strains TA 98, TA 100, TA 1535, TA 1537, and TA 1538 and in the Chinese Hamster Ovary (CHO) test for chromosomal aberrations, or in vivo in assays using mouse germinal cell chromosomes, Chinese hamster bone marrow chromosomes, and the Drosophila sex-linked recessive lethal trait gene. Positive test results were obtained only in the in vitro CHO Sister Chromatid Exchange (clastogenicity) and in the Mouse Lymphoma Cell (mutagenicity) assays, using concentrations of hydrochlorothiazide from 43 to 1300 mcg/mL, and in the Aspergillus nidulans non-disjunction assay at an unspecified concentration.

Hydrochlorothiazide had no adverse effects on the fertility of mice and rats of either sex in studies wherein these species were exposed, via their diet, to doses of up to 100 and 4 mg/kg, respectively, prior to mating and throughout gestation.

14 CLINICAL STUDIES

14.1 Losartan Monotherapy

Reduction in the Risk of Stroke: The LIFE study was a multinational, double-blind study comparing losartan and atenolol in 9193 hypertensive patients with ECG-documented left ventricular hypertrophy. Patients with myocardial infarction or stroke within six months prior to randomization were excluded. Patients were randomized to receive once daily losartan 50 mg or atenolol 50 mg. If goal blood pressure (<140/90 mmHg) was not reached, hydrochlorothiazide (12.5 mg) was added first and, if needed, the dose of losartan or atenolol was then increased to 100 mg once daily. If necessary, other antihypertensive treatments (e.g., increase in dose of hydrochlorothiazide therapy to 25 mg or addition of other diuretic therapy, calcium channel blockers, alpha-blockers, or centrally acting agents, but not ACE inhibitors, angiotensin II antagonists, or beta-blockers) were added to the treatment regimen to reach the goal blood pressure.

In efforts to control blood pressure, the patients in both arms of the LIFE study were coadministered hydrochlorothiazide the majority of time they were on study drug (73.9% and 72.4% of days in the losartan and atenolol arms, respectively).

Of the randomized patients, 4963 (54%) were female and 533 (6%) were Black. The mean age was 67 with 5704 (62%) age ≥65. At baseline, 1195 (13%) had diabetes, 1326 (14%) had isolated systolic hypertension, 1469 (16%) had coronary heart disease, and 728 (8%) had cerebrovascular disease. Baseline mean blood pressure was 174/98 mmHg in both treatment groups. The mean length of follow-up was 4.8 years. At the end of study or at the last visit before a primary endpoint, 77% of the group treated with losartan and 73% of the group treated with atenolol were still taking study medication. Of the patients still taking study medication, the mean doses of losartan and atenolol were both about 80 mg/day, and 15% were taking atenolol or losartan as monotherapy, while 77% were also receiving hydrochlorothiazide (at a mean dose of 20 mg/day in each group). Blood pressure reduction measured at trough was similar for both treatment groups but blood pressure was not measured at any other time of the day. At the end of study or at the last visit before a primary endpoint, the mean blood pressures were 144.1/81.3 mmHg for the group treated with losartan and 145.4/80.9 mmHg for the group treated with atenolol [the difference in SBP of 1.3 mmHg was significant (p<0.001), while the difference of 0.4 mmHg in DBP was not significant (p=0.098)].

The primary endpoint was the first occurrence of cardiovascular death, nonfatal stroke, or nonfatal myocardial infarction. Patients with nonfatal events remained in the trial, so that there was also an examination of the first event of each type even if it was not the first event (e.g., a stroke following an initial myocardial infarction would be counted in the analysis of stroke). Treatment with losartan resulted in a 13% reduction (p=0.021) in risk of the primary endpoint compared to the atenolol group; this difference was primarily the result of an effect on fatal and nonfatal stroke. Treatment with losartan reduced the risk of stroke by 25% relative to atenolol (p=0.001).

14.2 Losartan Potassium-Hydrochlorothiazide

The 3 controlled studies of losartan and hydrochlorothiazide included over 1300 patients assessing the antihypertensive efficacy of various doses of losartan (25, 50 and 100 mg) and concomitant hydrochlorothiazide (6.25, 12.5 and 25 mg). A factorial study compared the combination of losartan/hydrochlorothiazide 50/12.5 mg with its components and placebo. The combination of losartan/hydrochlorothiazide 50/12.5 mg resulted in an approximately additive placebo-adjusted systolic/diastolic response (15.5/9.0 mmHg for the combination compared to 8.5/5.0 mmHg for losartan alone and 7.0/3.0 mmHg for hydrochlorothiazide alone). Another study investigated the dose-response relationship of various doses of hydrochlorothiazide (6.25, 12.5 and 25 mg) or placebo on a background of losartan (50 mg) in patients not adequately controlled (Sitting Diastolic Blood Pressure [SiDBP] 93-120 mmHg) on losartan (50 mg) alone. The third study investigated the dose-response relationship of various doses of losartan (25, 50 and 100 mg) or placebo on a background of hydrochlorothiazide (25 mg) in patients not adequately controlled (SiDBP 93-120 mmHg) on hydrochlorothiazide (25 mg) alone. These studies showed an added antihypertensive response at trough (24 hours post-dosing) of hydrochlorothiazide 12.5 or 25 mg added to losartan 50 mg of 5.5/3.5 and 10.0/6.0 mmHg, respectively. Similarly, there was an added antihypertensive response at trough when losartan 50 or 100 mg was added to hydrochlorothiazide 25 mg of 9.0/5.5 and 12.5/6.5 mmHg, respectively. There was no significant effect on heart rate.

There was no difference in response for men and women or in patients over or under 65 years of age.

Black patients had a larger response to hydrochlorothiazide than non-Black patients and a smaller response to losartan. The overall response to the combination was similar for Black and non-Black patients.

Severe Hypertension (SiDBP ≥110 mmHg)

The safety and efficacy of HYZAAR as initial therapy for severe hypertension (defined as a mean SiDBP ≥110 mmHg confirmed on 2 separate occasions off all antihypertensive therapy) was studied in a 6-week double-blind, randomized, multicenter study. Patients were randomized to either losartan and hydrochlorothiazide (50/12.5 mg, once daily) or to losartan (50 mg, once daily) and followed for blood pressure response. Patients were titrated at 2-week intervals if their SiDBP did not reach goal (<90 mmHg). Patients on combination therapy were titrated from losartan 50 mg/hydrochlorothiazide 12.5 mg to losartan 50 mg/hydrochlorothiazide 12.5 mg (sham titration to maintain the blind) to losartan 100 mg/hydrochlorothiazide 25 mg. Patients on monotherapy were titrated from losartan 50 mg to losartan 100 mg to losartan 150 mg, as needed. The primary endpoint was a comparison at 4 weeks of patients who achieved goal diastolic blood pressure (trough SiDBP <90 mmHg).

The study enrolled 585 patients, including 264 (45%) females, 124 (21%) blacks, and 21 (4%) ≥65 years of age. The mean blood pressure at baseline for the total population was 171/113 mmHg. The mean age was 53 years. After 4 weeks of therapy, the mean SiDBP was 3.1 mmHg lower and the mean SiSBP was 5.6 mmHg lower in the group treated with HYZAAR. As a result, a greater proportion of the patients on HYZAAR reached the target diastolic blood pressure (17.6% for HYZAAR, 9.4% for losartan; p=0.006). Similar trends were seen when the patients were grouped according to gender, race or age (<, ≥ 65).

After 6 weeks of therapy, more patients who received the combination regimen reached target diastolic blood pressure than those who received the monotherapy regimen (29.8% versus 12.5%).

16 HOW SUPPLIED/STORAGE AND HANDLING

HYZAAR is supplied as a film-coated tablet.

Losartan/ Hydrochlorothiazide | Color | Shape | Engraving | NDC 78206-xxx-xx
Losartan/ Hydrochlorothiazide | Color | Shape | Engraving | Bottle/ 30 | Bottle/ 90
50/12.5 mg | yellow | oval | 717 | 139-01 | 139-02
100/12.5 mg | white | oval | 745 | 140-01 | 140-02
100/25 mg | light yellow | oval | 747 | 141-01 | 141-02

STORAGE AND HANDLING

Store at 77°F (25°C); excursions permitted to 59°F to 86°F (15°C to 30°C). Keep container tightly closed. Protect from light.

17 PATIENT COUNSELING INFORMATION

Advise the patient to read the FDA-approved patient labeling (Patient Information).

Pregnancy: Advise female patients of childbearing age about the consequences of exposure to HYZAAR during pregnancy. Discuss treatment options with women planning to become pregnant. Tell patients to report pregnancies to their physicians as soon as possible [see Warnings and Precautions (5.1) and Use in Specific Populations (8.1)].

Symptomatic Hypotension: Advise patients that lightheadedness can occur, especially during the first days of therapy, and to report this symptom to a healthcare provider. Inform patients that dehydration from inadequate fluid intake, excessive perspiration, vomiting, or diarrhea may lead to an excessive fall in blood pressure. If syncope occurs, advise patients to contact their healthcare provider [see Warnings and Precautions (5.2)].

Potassium Supplements: Advise patients not to use potassium supplements or salt substitutes containing potassium without consulting their healthcare provider [see Drug Interactions (7.1)].

Acute Myopia and Secondary Angle-closure Glaucoma: Advise patients to discontinue HYZAAR and seek immediate medical attention if they experience symptoms of acute myopia or secondary angle-closure glaucoma [see Warnings and Precautions (5.6)].

Non-melanoma Skin Cancer: Instruct patients taking hydrochlorothiazide to protect skin from the sun and undergo regular skin cancer screening.

Manufactured for: Organon LLC, a subsidiary of
ORGANON & Co.,
Jersey City, NJ 07302, USA

For patent information: www.organon.com/our-solutions/patent/

© 2025 Organon group of companies. All rights reserved.

uspi-og0954a-t-2506r002

Patient Information
HYZAAR®
(HY-zar)
(losartan potassium and hydrochlorothiazide tablets)
50/12.5 mg, 100/12.5 mg, 100/25 mg
Rx only

Read the Patient Information that comes with HYZAAR® before you start taking it and each time you get a refill. There may be new information. This leaflet does not take the place of talking with your doctor about your condition and treatment.

What is the most important information I should know about HYZAAR?

- HYZAAR can cause harm or death to an unborn baby.
- Talk to your doctor about other ways to lower your blood pressure if you plan to become pregnant.
- If you get pregnant while taking HYZAAR tell your doctor right away.

What is HYZAAR?

HYZAAR contains 2 prescription medicines, an angiotensin receptor blocker (ARB) and a diuretic (water pill). It is used to:

- lower high blood pressure (hypertension). HYZAAR is not usually the first medicine used to treat high blood pressure.
- lower the chance of stroke in patients with high blood pressure and a heart problem called left ventricular hypertrophy (LVH). HYZAAR may not help Black patients with this problem.

HYZAAR has not been studied in children less than 18 years old.

High Blood Pressure (hypertension). Blood pressure is the force in your blood vessels when your heart beats and when your heart rests. You have high blood pressure when the force is too much. The losartan ingredient in HYZAAR can help your blood vessels relax so your blood pressure is lower. The hydrochlorothiazide ingredient in HYZAAR works by making your kidneys pass more water and salt.

Left Ventricular Hypertrophy (LVH) is an enlargement of the walls of the left chamber of the heart (the heart's main pumping chamber). LVH can happen from several things. High blood pressure is the most common cause of LVH.

Who should not take HYZAAR?

Do not take HYZAAR if you:

- are allergic to any ingredients in HYZAAR. See a complete list of ingredients in HYZAAR at the end of this leaflet.
- are not passing urine.
- have diabetes and are taking a medicine called aliskiren to reduce blood pressure.

What should I tell my doctor before taking HYZAAR?

Tell your doctor about all your medical conditions including if you:

- are pregnant or planning to become pregnant. See "What is the most important information I should know about HYZAAR?"
- are breastfeeding or plan to breastfeed. HYZAAR can pass into your milk and may harm your baby. You and your doctor should decide if you will take HYZAAR or breastfeed. You should not do both.
- have been vomiting (throwing up), having diarrhea, sweating a lot, or not drinking enough fluids. These could cause you to have low blood pressure.
- have liver problems
- have kidney problems
- have systemic lupus erythematosus (Lupus; SLE)
- have diabetes
- have gout
- have any allergies
- have had skin cancer or if you develop a new skin lesion during the treatment. Treatment with hydrochlorothiazide may increase the risk of some types of skin cancer (non-melanoma skin cancer). Discuss with your doctor how to protect your skin from sun exposure and how often you should undergo skin cancer screening.

Tell your doctor about all of the medicines you take, including prescription and non-prescription medicines, vitamins, and herbal supplements.

HYZAAR and certain other medicines may interact with each other. Especially tell your doctor if you are taking:

- potassium supplements
- salt substitutes containing potassium
- other medicines that may increase serum potassium
- water pills (diuretics)
- lithium (a medicine used to treat a certain kind of depression)
- medicines used to treat pain and arthritis, called non-steroidal anti-inflammatory drugs (NSAIDs), including COX-2 inhibitors
- other medicines to reduce blood pressure.

Know the medicines you take. Keep a list of your medicines and show it to your doctor and pharmacist when you get a new medicine.

How should I take HYZAAR?

- Take HYZAAR exactly as prescribed by your doctor. Your doctor may change your dose if needed.
- HYZAAR can be taken with or without food.
- If you miss a dose, take it as soon as you remember. If it is close to your next dose, do not take the missed dose. Just take the next dose at your regular time.
- If you take too much HYZAAR, call your doctor or Poison Control Center, or go to the nearest hospital emergency room right away.
- Your doctor may do blood tests from time to time while you are taking HYZAAR.

What are the possible side effects of HYZAAR?

HYZAAR may cause the following side effects that may be serious:

- Injury or death of unborn babies. See "What is the most important information I should know about HYZAAR?"
- Allergic reaction. Symptoms of an allergic reaction are swelling of the face, lips, throat, or tongue and may include severe shortness of breath and/or difficulty breathing. Get emergency medical help right away and stop taking HYZAAR.
- Low blood pressure (hypotension). Low blood pressure may cause you to feel faint or dizzy. Lie down if you feel faint or dizzy. Call your doctor right away.
- If you have kidney problems, you may see a worsening in how well your kidneys work. Call your doctor if you get swelling in your feet, ankles, or hands, or unexplained weight gain.
- A new or worsening condition called systemic lupus erythematosus (Lupus; SLE)
- Eye problems. One of the medicines in HYZAAR can cause eye problems that, if left untreated, may lead to vision loss. Symptoms of eye problems can happen within hours to weeks of starting HYZAAR. Tell your doctor right away if you have:
  - decrease in vision
  - eye pain
- Sensitivity of the skin to the sun and risk of skin cancer.

The most common side effects of HYZAAR in people with high blood pressure are:

- "colds" (upper respiratory infection)
- dizziness
- stuffy nose
- back pain

Tell your doctor if you get any side effect that bothers you or that won't go away. This is not a complete list of side effects. For a complete list, ask your doctor or pharmacist.

How should I store HYZAAR?

- Store HYZAAR at room temperature at 59°F to 86°F (15°C to 30°C).
- Keep HYZAAR in a tightly closed container, and keep HYZAAR out of the light.
- Keep HYZAAR and all medicines out of the reach of children.

General information about HYZAAR

Medicines are sometimes prescribed for conditions that are not mentioned in patient information leaflets. Do not use HYZAAR for a condition for which it was not prescribed. Do not give HYZAAR to other people, even if they have the same symptoms that you have. It may harm them.

This leaflet summarizes the most important information about HYZAAR. If you would like more information, talk with your doctor. You can ask your pharmacist or doctor for information that is written for health professionals.

What are the ingredients in HYZAAR?

Active ingredients: losartan potassium, hydrochlorothiazide

Inactive ingredients:

microcrystalline cellulose, lactose hydrous, pregelatinized starch, magnesium stearate, hydroxypropyl cellulose, hypromellose, titanium dioxide. HYZAAR 50/12.5 and HYZAAR 100/25 also contain D&C yellow No. 10 aluminum lake.

HYZAAR 50/12.5, HYZAAR 100/12.5, and HYZAAR 100/25 may also contain carnauba wax.

Manufactured for: Organon LLC, a subsidiary of
ORGANON & Co.,
Jersey City, NJ 07302, USA

For patent information: www.organon.com/our-solutions/patent/

© 2023 Organon group of companies. All rights reserved.

Revised: 3/2023

usppi-og0954a-t-2303r001

PRINCIPAL DISPLAY PANEL - 50 mg/12.5 mg Tablet Bottle Label

NDC 78206-139-01

Hyzaar®
(Losartan Potassium and
Hydrochlorothiazide Tablets)

50 mg/12.5 mg

Each tablet contains 50 mg losartan potassium and
12.5 mg hydrochlorothiazide.
Store at 77°F (25°C); excursions permitted to
59°F to 86°F (15°C to 30°C).
Keep container tightly closed. Protect from light.

Rx only

30 Tablets

PRINCIPAL DISPLAY PANEL - 100 mg/12.5 mg Tablet Bottle Label

NDC 78206-140-01

Hyzaar®
(Losartan Potassium and
Hydrochlorothiazide Tablets)

100 mg/12.5 mg

Each tablet contains 100 mg losartan potassium and
12.5 mg hydrochlorothiazide.
Store at 77°F (25°C); excursions permitted to
59°F to 86°F (15°C to 30°C).
Keep container tightly closed. Protect from light.

Rx only

30 Tablets

PRINCIPAL DISPLAY PANEL - 100 mg/25 mg Tablet Bottle Label

NDC 78206-141-01

Hyzaar®
(Losartan Potassium and
Hydrochlorothiazide Tablets)

100 mg/25 mg

Each tablet contains 100 mg losartan potassium and
25 mg hydrochlorothiazide.
Store at 77°F (25°C); excursions permitted to
59°F to 86°F (15°C to 30°C).
Keep container tightly closed. Protect from light.

Rx only

30 Tablets